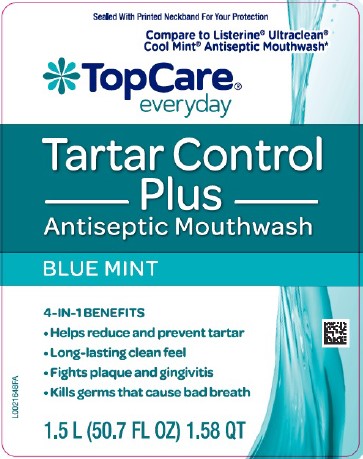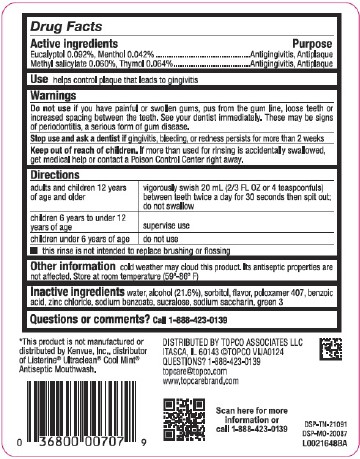 DRUG LABEL: Tartar control plus Antiseptic
NDC: 76162-855 | Form: MOUTHWASH
Manufacturer: Topco Associates LLC
Category: otc | Type: HUMAN OTC DRUG LABEL
Date: 20260213

ACTIVE INGREDIENTS: EUCALYPTOL 0.92 mg/1 mL; MENTHOL 0.42 mg/1 mL; METHYL SALICYLATE 0.6 mg/1 mL; THYMOL 0.64 mg/1 mL
INACTIVE INGREDIENTS: SODIUM BENZOATE; SUCRALOSE; SACCHARIN SODIUM; FD&C GREEN NO. 3; WATER; ALCOHOL; SORBITOL; POLOXAMER 407; BENZOIC ACID; ZINC CHLORIDE

Top Care 855.000/855AA-AC
Tartar Control Plus Antiseptic Mouth Rinse, Blue Mint

Active ingredients

Eucalyptol 0.092%

Menthol 0.042%

Methyl salicylate 0.060%,

Thymol 0.064%

Purpose

Antigingivitis, Antiplaque

Use

helps control plaque that leads to gingivitis

Warnings

for this product

Do not use

if you have painful or swollen gums, pus from the gum line, loose teeth or increased spacing between the teeth. See your dentist immediately. These may be signs of periodontitis, a serious form of gum disease.

Stop use and ask a dentist if

gingivitis, bleeding, or redness persists for more than 2 weeks

Keep out of reach of children.

If more than used for rinsing is accidentally swallowed, get medical help or contact a Poison Control Center right away.

Directions

adults and children 12 years of age and older - vigorously swish 20 mL (2/3 FL OZ or 4 teaspoonfuls) between teeth twice a day for 30 seconds then spit out; do not swallow

children 6 years to under 12 years of age - supervise use

children under 6 years of age - do not use

- this rinse is not intended to replace brushing or flossing

Other information

cold weather may cloud this product. Its antiseptic properties are not affected. Store at room temperature (59°to 86°F).

Inactive ingredients

water, alcohol (21.6%), sorbitol, flavor, poloxamer 407, benzoic acid, zinc chloride, sodium benzoate, sucralose, sodium saccharin, green 3

Questions or comments?

Call 1-888-423-0139

Disclaimer

*This product is not manufactured or distributed by Kenvue, Inc., distributor of Listerine®Ultraclean®Cool Mint®Antiseptic Mouthwash.

Adverse reaction

DISTRIBUTED BY TOPCO ASSOCIATES LLC

ITASCA, IL 60143 ©TOPCO vija0124

QUESTIONS? 1-888-423-0139

topcare@topco.com

www.topcarebrands.com

Scan here for more information or call 1-888-423-0139

DSP-TN-21091

DSP-MO-20087

PRINCIPAL DISPLAY PANEL

Sealed With Printed Neckband For Your Protection

Compare to Listerine®Ultraclean®Cool Mint®Antiseptic Mouthwash*

TopCare®everyday

Tartar Control Plus

Antiseptic Mouthwash

BLUE MINT

4-IN-1 BENEFITS

- Helps reduce and prevent tartar
- Long-lasting clean feel
- Fights plaque and gingivitis
- Kills germs that cause bad breath

1.5 L (50.7 FL OZ) 1.58 QT